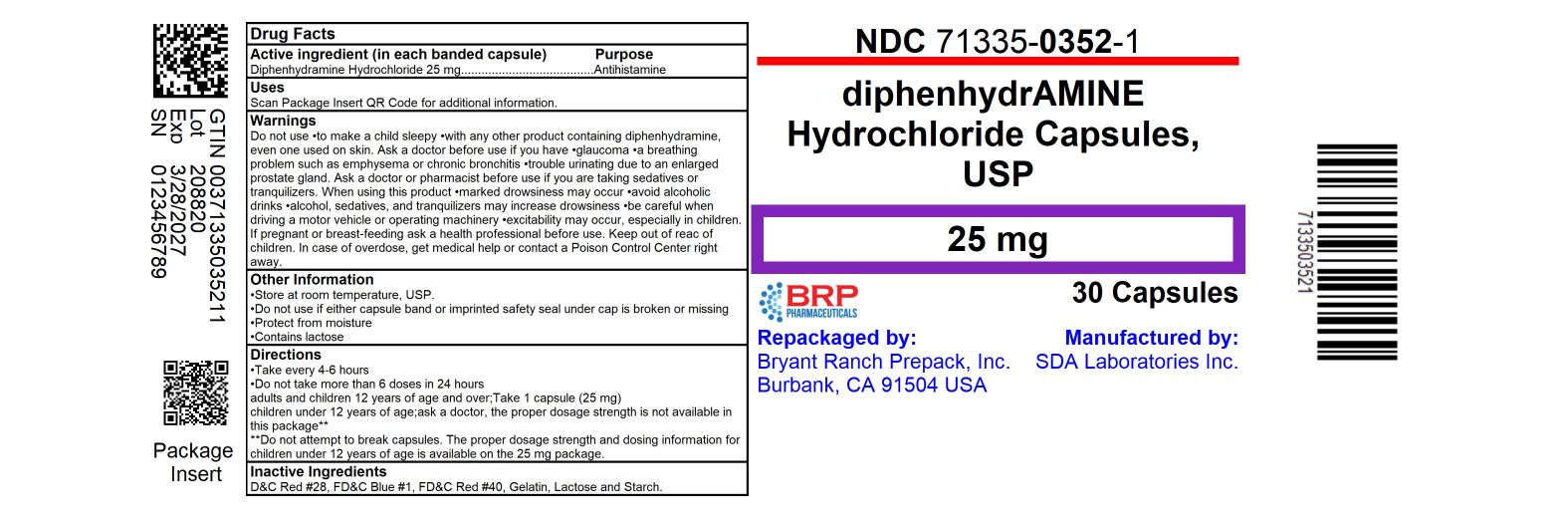 DRUG LABEL: Diphenhydramine HCL
NDC: 71335-0352 | Form: CAPSULE
Manufacturer: Bryant Ranch Prepack
Category: otc | Type: HUMAN OTC DRUG LABEL
Date: 20250328

ACTIVE INGREDIENTS: DIPHENHYDRAMINE HYDROCHLORIDE 25 mg/1 1
INACTIVE INGREDIENTS: FERROSOFERRIC OXIDE; D&C RED NO. 28; FD&C BLUE NO. 1; FD&C RED NO. 40; GELATIN, UNSPECIFIED; LACTOSE MONOHYDRATE; MAGNESIUM STEARATE; SILICON DIOXIDE; SODIUM LAURYL SULFATE

Drug Facts

Active ingredient (in each capsule)

Diphenhydramine HCL 25 mg

Purpose

Antihistamine

Uses:

Temporarily relieves these symptoms associated with the common cold, hay fever, or other respiratory allergies.

- sneezing
- nasal congestion
- runny nose
- itchy, watery eyes

Do not use

- With any other product containing Diphenhydramine HCL, including one applied topically.

Ask a doctor or pharmacist before use

If you have

- trouble urinating due to enlarged prostate gland
- a breathing problem such as emphysema or chronic bronchitis
- glaucoma
- if you are taking sedatives or tranquilizers

When using this product

- aAvoid alcoholic drinks.
- marked drowsiness may occur.
- excitability may occur, especially in children.
- alcohol, sedatives and tranquilizers may increase drowsiness.
- be careful when driving a motor vehicle or operating machinery.

If pregnant or breast-feeding,

ask a health professional before use.

Keep out of reach of children

In case of overdose, get medical help or contact a Poison Control Center right away.

Directions:

- Take every 4-6 hours
- Do not take more than 6 doses in 24 hours.

Adults and children 12 years or over | 1 to 2 capsule
Children 6 to under 12 years | 1 capsule
Children under 6 years | ask a doctor

Other information:

- Store at room temperature 15-30 degrees C (59-86 degrees F)
- Protect from excessive moisture

HOW SUPPLIED

Diphenhydramine HCl 25 mg

- NDC: 71335-0352-1: 30 Capsules in a BOTTLE
- NDC: 71335-0352-2: 20 Capsules in a BOTTLE
- NDC: 71335-0352-3: 42 Capsules in a BOTTLE
- NDC: 71335-0352-4: 24 Capsules in a BOTTLE
- NDC: 71335-0352-5: 15 Capsules in a BOTTLE
- NDC: 71335-0352-6: 60 Capsules in a BOTTLE
- NDC: 71335-0352-7: 10 Capsules in a BOTTLE
- NDC: 71335-0352-8: 6 Capsules in a BOTTLE
- NDC: 71335-0352-9: 90 Capsules in a BOTTLE
- NDC: 71335-0352-0: 100 Capsules in a BOTTLE

Repackaged/Relabeled by:
Bryant Ranch Prepack, Inc.
Burbank, CA 91504

PACKAGE LABEL

Diphenhydramine HCl Capsules 25 mg